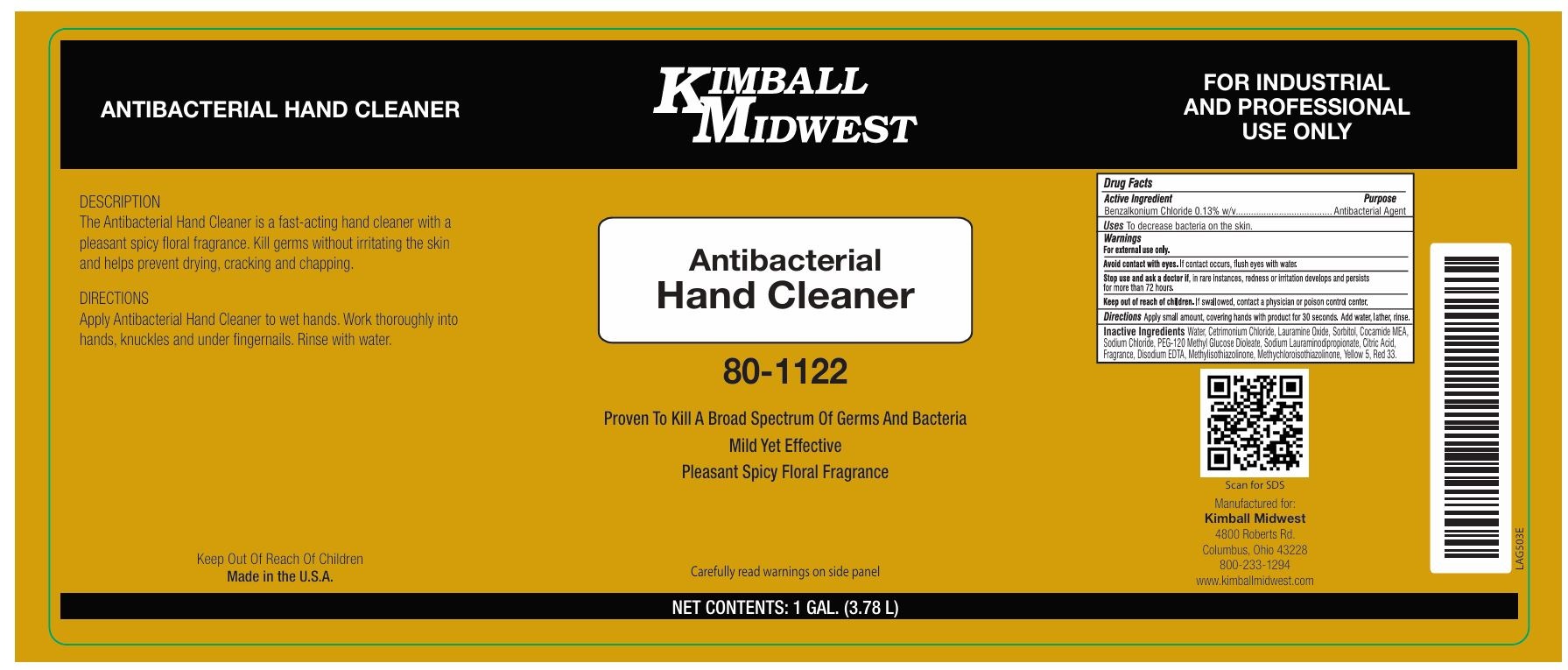 DRUG LABEL: KIMBALL MIDWEST Antibacterial Hand Cleaner
NDC: 66608-216 | Form: LIQUID
Manufacturer: Kimball Midwest
Category: otc | Type: HUMAN OTC DRUG LABEL
Date: 20241106

ACTIVE INGREDIENTS: BENZALKONIUM CHLORIDE 1.3 mg/1 mL
INACTIVE INGREDIENTS: WATER; CETRIMONIUM CHLORIDE; LAURAMINE OXIDE; SORBITOL; COCO MONOETHANOLAMIDE; SODIUM CHLORIDE; PEG-120 METHYL GLUCOSE DIOLEATE; SODIUM LAURIMINODIPROPIONATE; CITRIC ACID MONOHYDRATE; EDETATE DISODIUM; METHYLISOTHIAZOLINONE; METHYLCHLOROISOTHIAZOLINONE; FD&C YELLOW NO. 5; D&C RED NO. 33

KIMBALL MIDWEST Antibacterial Hand Cleaner

Active Ingredient

Benzalkonium Chloride 0.13% w/v

Purpose

Antibacterial Agent

Uses

To decrease bacteria on the skin.

Warnings

For external use only.

Avoid contact with eyes. If contact occurs, flush eyes with water.

Stop use and ask a doctor if, in rare instances, redness or irritation develops and persists for more than 72 hours.

Keep out of reach of children. If swallowed, contact a physician or poison control center.

Directions

Apply small amount, covering hands with product for 30 seconds. Add water, lather, rinse.

Inactive Ingredients

Water, Cetrimonium Chloride, Lauramine Oxide, Sorbitol, Cocamide MEA, Sodium Chloride, PEG-120 Methyl Glucose Dioleate, Sodium Lauraminodipropionate, Citric Acid, Fragrance, Disodium EDTA, Methylisothiazolinone, Methychloroisothiazolinone, Yellow 5, Red 33.

Proven To Kill A Broad Spectrum Of Germs And Bacteria

Mild Yet Effective

Pleasant Spicy Floral Fragrance

Carefully read warnings on side panel

FOR INDUSTRIAL AND PROFESSIONAL USE ONLY

Manufactured for:
Kimball Midwest
4800 Roberts Rd.
Columbus, Ohio 43228
800-233-1294
www.kimballmidwest.com

DESCRIPTION
The Antibacterial Hand Cleaner is a fast-acting hand cleaner with a pleasant spicy floral fragrance. Kill germs without irritating the skin and helps prevent drying, cracking and chapping.

DIRECTIONS
Apply Antibacterial Hand Cleaner to wet hands. Work thoroughly into hands, knuckles and under fingernails. Rinse with water.

Made in the U.S.A.